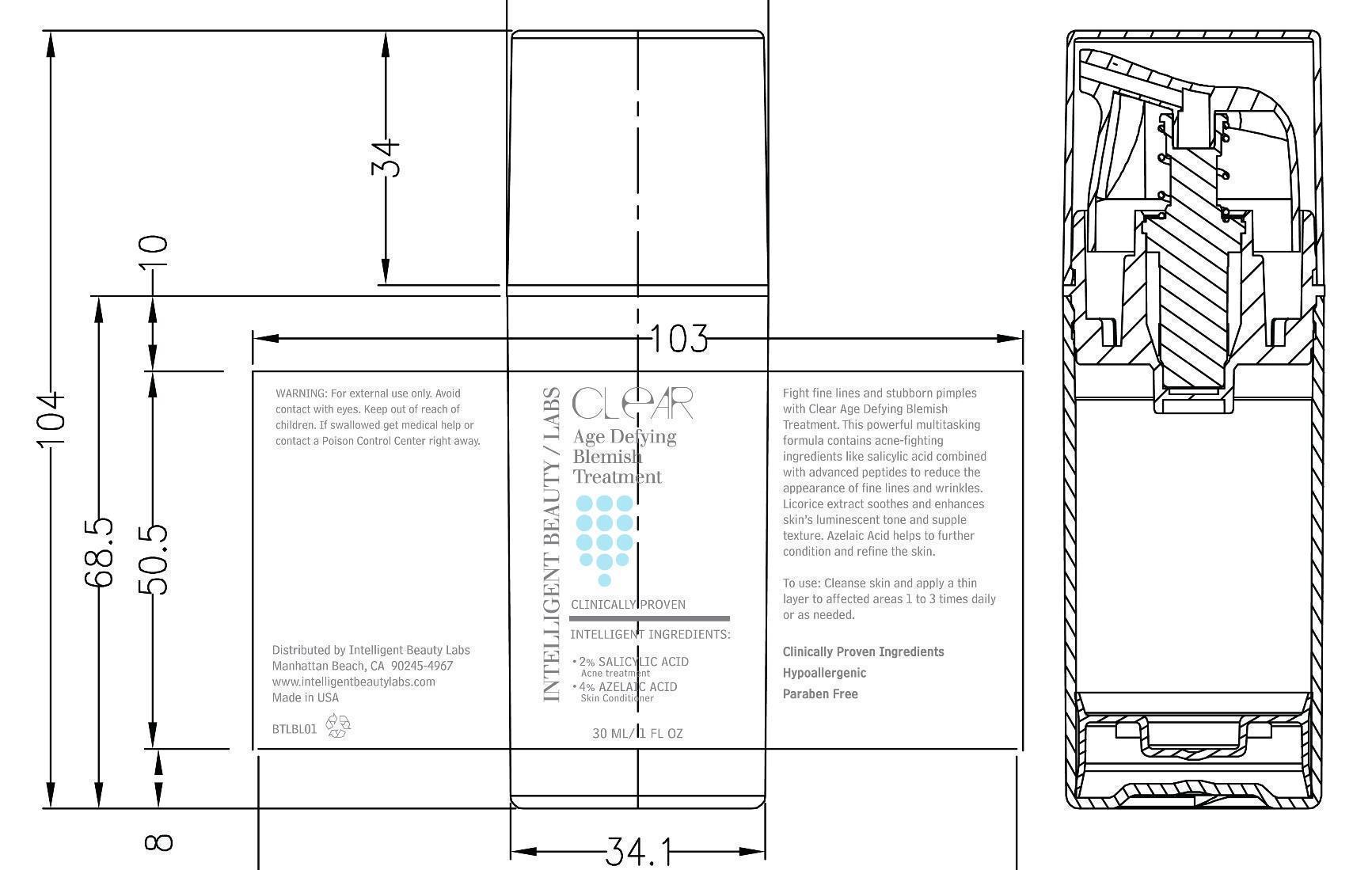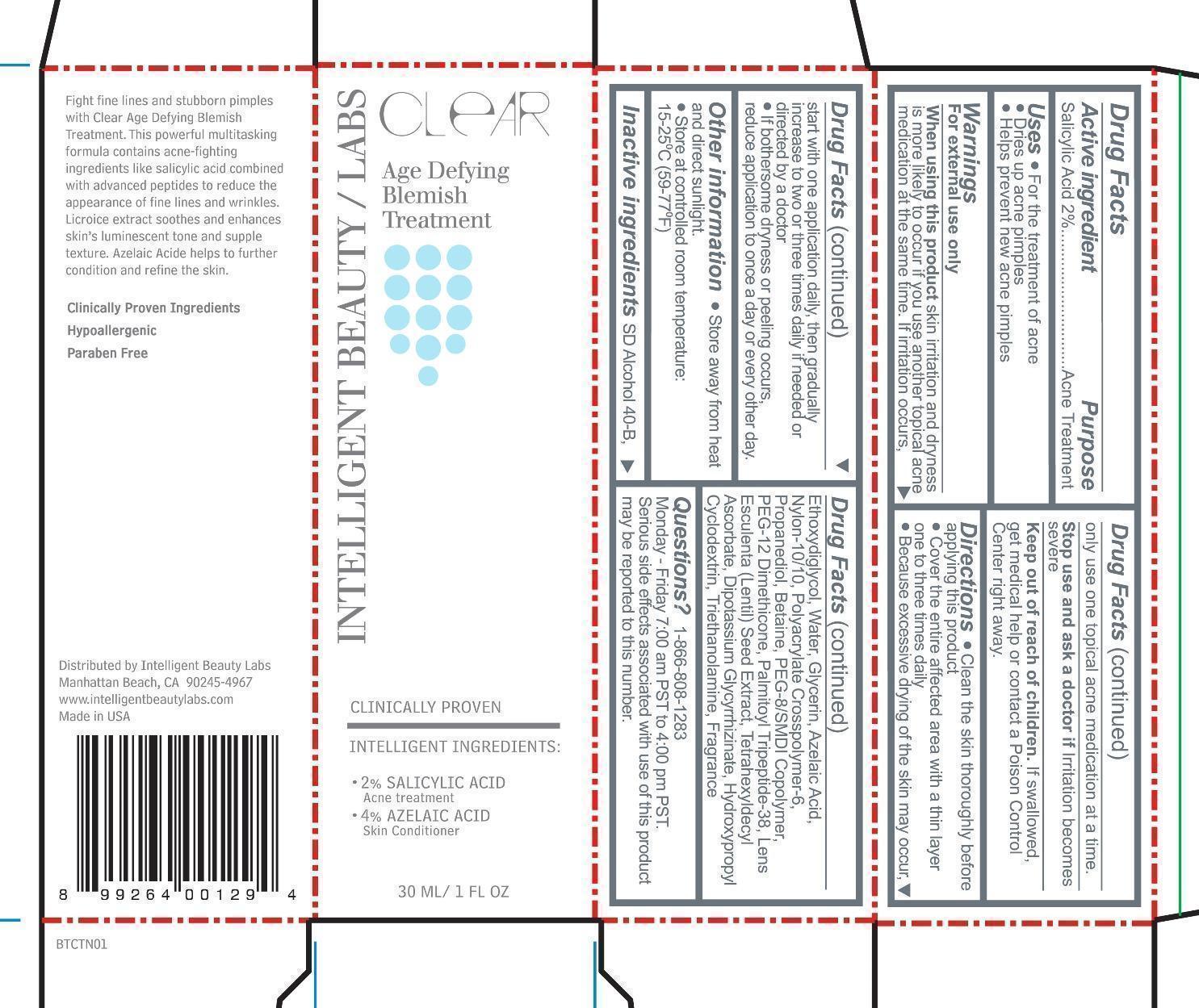 DRUG LABEL: Age Defying Blemish Treatment
NDC: 44717-148 | Form: cream
Manufacturer: Wasatch Product Development, LLC
Category: otc | Type: HUMAN OTC DRUG LABEL
Date: 20150212

ACTIVE INGREDIENTS: SALICYLIC ACID 2 g/100 mL
INACTIVE INGREDIENTS: ALCOHOL; DIETHYLENE GLYCOL MONOETHYL ETHER; WATER; GLYCERIN; AZELAIC ACID; PROPANEDIOL; BETAINE; PEG-8/SMDI COPOLYMER; PEG-12 DIMETHICONE (300 CST); LENTIL; TETRAHEXYLDECYL ASCORBATE; GLYCYRRHIZINATE DIPOTASSIUM; HYDROXYPROPYL .ALPHA.-CYCLODEXTRIN; TROLAMINE

Clear Age Defying Blemish Treatment

Active Ingredient Purpose

Salicylic Acid 2% Acne Treatment

Uses

For the treatment of acne

Dries up acne pimples

Helps prevent new acne pimples

Keep out of reach of children. If swallowed, get medical help or contact a a Poison Control Center right away.

Stop use and ask a doctor if irritation becomes severe.

Warnings

For external use only

When using this product skin irritation and dryness is more likely to occur if you use another topical acne medication. If irritation occurs, start with one application daily, then gradually increase to two or three times daily if needed or directed by a doctor.

If bothersome dryness or peeling occurs, reduce application to once a day or every other day.

Directions

Clean the skin thoroughly before applying this product

Cover the entire affected area with a thin layer one to three times daily

Becuase excessive drying of the skin may occur, start with one application daily, then gradually increase to two or three daily if needed or directed by a doctor.

INACTIVE INGREDIENT

Inactive ingredients SD Alcohol 40-B, Ethoxydiglycol, Water, Glycerin, Azelaic Acid, Nylon-10/10, Polyacrylate Crosspolymer-6, Propanediol, Betaine, PEG-8/SMDI Copolymer, PEG-12 Dimethicone, Palmitoyl Tripeptide-38, Lens Esculenta (Lentil) Seed Extract, Tetrahexyldecyl Ascorbate, Dipotassium Glycyrrhizinate, Hydroxypropyl Cyclodextrin, Triethanolamine, Fragrance

PACKAGE LABEL

Clear

Age Defying Treatment

2% Salicylic Acid

Acne Treatment

4% Azelaic Acid

Skin Conditioner

30 ML/ 1 FL OZ